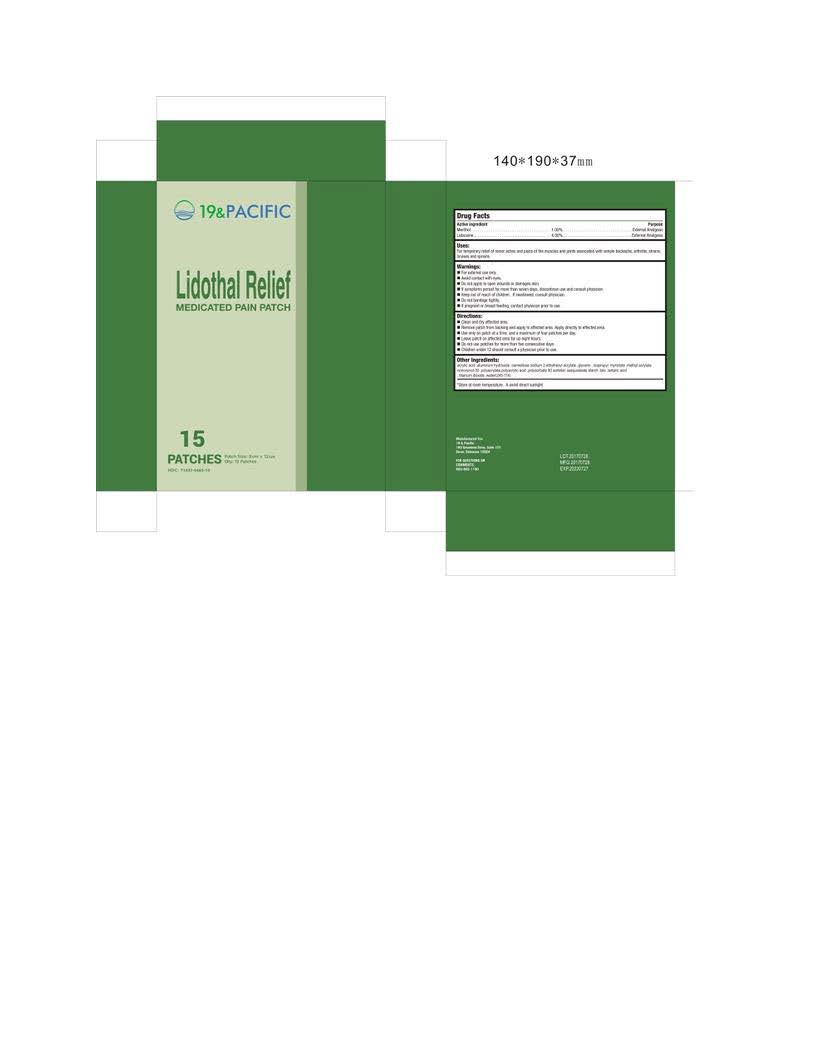 DRUG LABEL: Lidothal Relief
NDC: 71437-463 | Form: PATCH
Manufacturer: 19 And Pacific, Llc
Category: otc | Type: HUMAN OTC DRUG LABEL
Date: 20170731

ACTIVE INGREDIENTS: MENTHOL 1 g/100 g; LIDOCAINE 4 g/100 g
INACTIVE INGREDIENTS: ACRYLIC ACID; ALUMINUM HYDROXIDE; CROSCARMELLOSE SODIUM; 2-ETHYLHEXYL ACRYLATE; GLYCERIN; ISOPROPYL MYRISTATE; METHYL ACRYLATE; NONOXYNOL-30; POLYACRYLAMIDE (10000 MW); POLYACRYLIC ACID (250000 MW); POLYSORBATE 80; TALC; TARTARIC ACID; TITANIUM DIOXIDE; WATER

Drug Facts

Active Ingredient

Menthol 1.00%

Lidocaine 4.00%

Purpose

External analgesic

External analgesic

Uses:

For temporary relief of minor aches and pains of the muscles and joints associated with simple backache, arthritis, strains,

bruises and sprains

Warnings:

- For external use only
- Avoid contact with eyes
- Do not apply to open wounds or damages skin
- If symptoms persist for more than seven days, discontinue use and consult physician
- Keep out of reach of children. If swallowed, consult physician.
- Do not bandage tightly
- If pregnant or breast feeding, contact physician prior to use

Keep out of reach of children. If swallowed, consult physician.

Directions:

- Clean and dry affected area
- Remove patch from backing and apply to affected area. Apply directly to affected area.
- Use only on patch at a time, and a maximum of four patches per day.
- Leave patch of affected area for up to eight hours.
- Do not use patches for more than five consecutive days
- Children under 12 should consult a physician prior to use.

STORAGE AND HANDLING

Store at room temperature. Avoid direct sunlight.

INACTIVE INGREDIENT

Other Ingredients:

acrylic acid ,aluminum hydroxide . carmellose sodium 2-ethylexyl acrylate glycerin . isopropyl myristate .methyl acrylate

nonoxynol-30 .poluacrylate.polyacrylic acid .polysorbate 80 sorbitan sesquioleate strach .talc .tartaric acid

.titanium dioxide .water(254-114)